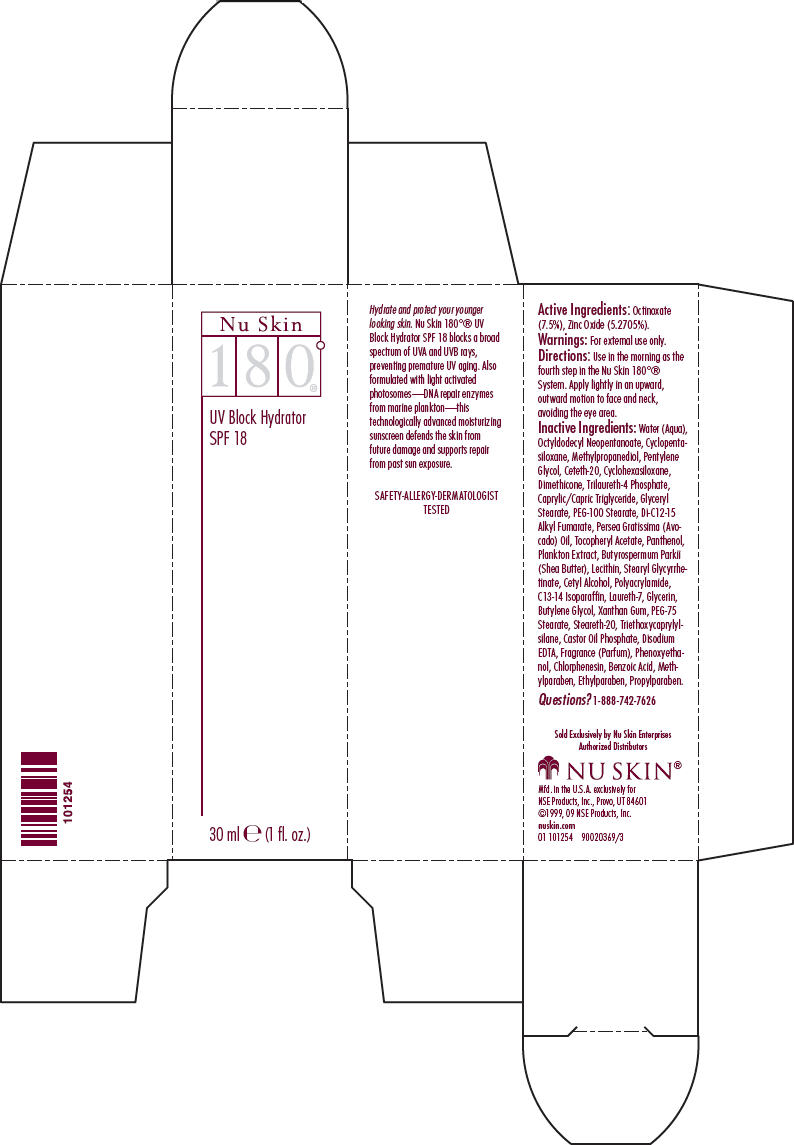 DRUG LABEL: Nu Skin 180 Degree UV Block Hydrator SPF 18
NDC: 62839-0125 | Form: LOTION
Manufacturer: NSE Products, Inc.
Category: otc | Type: HUMAN OTC DRUG LABEL
Date: 20181220

ACTIVE INGREDIENTS: Octinoxate 75 mg/1 mL; Zinc Oxide 52.705 mg/1 mL
INACTIVE INGREDIENTS: Water; Octyldodecyl Neopentanoate; Cyclomethicone 5; Methylpropanediol; Pentylene Glycol; Ceteth-20; Cyclomethicone 6; Dimethicone; Medium-Chain Triglycerides; Glyceryl Monostearate; Peg-100 Stearate; Avocado; PANTHENOL; Shea Butter; Cetyl Alcohol; C13-14 Isoparaffin; Laureth-7; Glycerin; Butylene Glycol; Xanthan Gum; PEG-75 Stearate; Steareth-20; Triethoxycaprylylsilane; Edetate Disodium; Phenoxyethanol; Chlorphenesin; Benzoic Acid; Methylparaben; Ethylparaben; Propylparaben

Nu Skin
180°®
UV Block Hydrator

Active Ingredients

Octinoxate (7.5%), Zinc Oxide (5.2705%).

Warnings

For external use only.

Directions

Use in the morning as the fourth step in the Nu Skin 180°® System. Apply lightly in an upward, outward motion to face and neck, avoiding the eye area.

Inactive Ingredients

Water (Aqua), Octyldodecyl Neopentanoate, Cyclopentasiloxane, Methylpropanediol, Pentylene Glycol, Ceteth-20, Cyclohexasiloxane, Dimethicone, Trilaureth-4 Phosphate, Caprylic/Capric Triglyceride, Glyceryl Stearate, PEG-100 Stearate, Di-C12-15 Alkyl Fumarate, Persea Gratissima (Avocado) Oil, Tocopheryl Acetate, Panthenol, Plankton Extract, Butyrospermum Parkii (Shea Butter), Lecithin, Stearyl Glycyrrhetinate, Cetyl Alcohol, Polyacrylamide, C13-14 Isoparaffin, Laureth-7, Glycerin, Butylene Glycol, Xanthan Gum, PEG-75 Stearate, Steareth-20, Triethoxycaprylylsilane, Castor Oil Phosphate, Disodium EDTA, Fragrance (Parfum), Phenoxyethanol, Chlorphenesin, Benzoic Acid, Methylparaben, Ethylparaben, Propylparaben.

Questions?

1-888-742-7626

PRINCIPAL DISPLAY PANEL - 30 ml Carton

Nu Skin
180°®

UV Block Hydrator
SPF 18

30 ml e (1 fl. oz.)